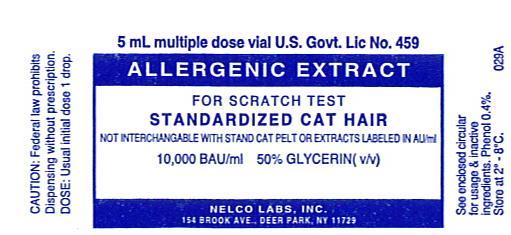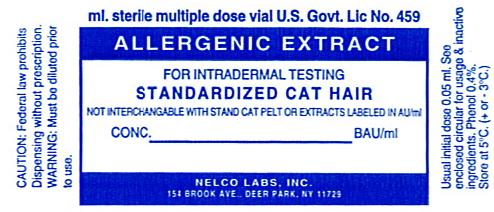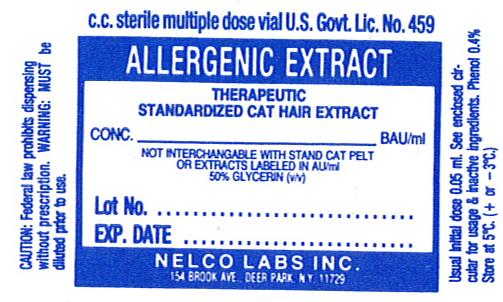 DRUG LABEL: Standardized Cat Hair
NDC: 36987-1121 | Form: INJECTION, SOLUTION
Manufacturer: Nelco Laboratories, Inc.
Category: prescription | Type: HUMAN PRESCRIPTION DRUG LABEL
Date: 20091207

ACTIVE INGREDIENTS: FELIS CATUS HAIR 10000 [BAU]/1 mL
INACTIVE INGREDIENTS: SODIUM CHLORIDE; SODIUM PHOSPHATE, DIBASIC; POTASSIUM PHOSPHATE, MONOBASIC; PHENOL; WATER; GLYCERIN

Allergenic Extract

WARNINGS

Standardized allergenic extract is intended for use by physicians who are experienced in the administration of standardized (BAU/mL) allergenic extracts for immunotherapy and the emergency care of anaphylaxis, or for use under the guidance of an allergy specialist. Standardized allergenic extracts are not directly interchangeable with other allergenic extracts. The initial dose must be based on skin testing as described in the dosage and administration section of this insert. Patients being switched from other types of extract to standardized allergenic extracts should be started as though they were coming under treatment for the first time. STANDARDIZED CAT HAIR EXTRACT IS NOT INTERCHANGEABLE WITH STANDARDIZED CAT PELT EXTRACTS, STANDARDIZED CAT EXTRACTS LABELED IN AU/mL, OR WITH NON-STANDARDIZED CAT EXTRACTS.

This product should not be injected intravenously. Deep subcutaneous routes have been safe. Sensitive patients may experience severe anaphylactic reactions resulting in respiratory obstruction, shock, coma and/or death. (See Adverse Reactions)

Serious adverse reactions should be reported to Nelco Laboratories immediately and a report filed to: MedWatch, The FDA Medical Product Problem Reporting Program, at 5600 Fishers Lane, Rockville, Md. 20852-9787, call 1-800-FDA-1088.

Extreme caution should be taken when using allergenic extracts for patients who are taking beta-blocker medications. In the event of a serious adverse reaction associated with the use of allergenic extracts, patients receiving beta-blockers may not be responsive to epinephrine or inhaled brochodialators. (See Precautions)

Allergenic extracts may be used with caution for patients with unstable or steroid-dependent asthma or with underlying cardiovascular disease. (See Contraindications)

DESCRIPTION

Standardized cat hair extract is a sterile glycerinated injectable solution containing the extractables of dried, powdered cat hair, wash and dander and 0.5% NaCl, 0.08% Na2HPO4, 0.036% KH2PO4, water for injection and 0.4%, phenol as preservative in sterile containers. All extracts are aseptically filled. Standardized cat hair extract is to be administered by prick-puncture or intradermal routes when used for diagnostic purposes and administered subcutaneously when used for immunotherapy injections.

The Bioequivalent Allergy Unit (BAU) nomenclature, now used for all Standardized Cat Extracts, replaces the previous Allergy Unit (AU) nomenclature for these products. Bioequivalent Allergy Units are based on quantitative intradermal skin test results and are intended to assure that the labeled unit of different allergenic extracts will correspond to the expected clinical response in sensitive patients. References labeled 10,000 BAU/mL can be diluted to one half million fold to produce an intradermal sum of erythema diameter response of 50 mm in highly puncture reactive subjects.

In vitro assignment of BAU/mL to this product is based on radial immunodiffusion (RID) assay results according to guidelines established by the Center for Biologics Evaluation and Research (CBER) as indicated below.(5, 6)

RID Cat 1 (Fel d I) /mL | BAU/mL | AU/mL
5.0 to 9.9 | 5,000 | 50,000
10.0 to 19.9 | 10,000 | 100,000

Bioequivalent Allergy Units (BAU) are NOT interchangeable with Allergy Units (AU). Standardized Cat Hair extract labeled in BAU/mL are not interchangeable with standardized cat pelt extracts or with cat hair extracts labeled in AU/mL or with non-standardized cat hair extracts.

It has been recognized through investigation that the allergens responsible for Cat allergy are found in the pelt, hair, dander, saliva, serum and urine.(1) Saliva especially when deposited on and in combination with the hair, root hairs and skin can produce a significant allergic reaction. Repeated surface washing of the animal proved significant enough so that the wash was added to the whole of the raw material producing the cat allergenic extract.(2,3,4) However the amount of Fel d 1 varies widely from animal to animal so it is an advantage to use raw material with a known amount of the antigen. Nelco's raw material, supplied by Biopol Laboratory, is dried, powdered cat hair, wash and dander, labeled with the number of Fel d 1 units in each gram of dried material per container. The raw material is extracted with a 50%(v/v) glycerinated diluent containing glycerin and 0.5% NaCl, 0.08% Na2HPO4, 0.036% KH2PO4, WFI, and 0.4% phenol as a preservative. Although extracts from whole pelts of cats are similar in content of Fel d 1 to extracts prepared only from wash, hair and dander, pelt extracts may contain other non-Fel d 1 allergenic molecules.

CLINICAL PHARMACOLOGY

The mode of action of allergenic extracts is still under investigation. The pharmacological action of allergenic extracts used diagnostically is based on the liberation of histamine and other substances when the allergen reacts with IgE antibodies attached to the mast cells.(11) The pharmacological action of allergenic extracts used for immunotherapy is based on an increase of IgG antibodies and allergen-specific T lymphocyte cells.

a. Prick-puncture tests on Cat allergic subjects: 11 puncture tests (bifurcated needle) on cat allergic subjects yielded the following:

# Persons | Mean sum of wheal (mm) | Range of sum of wheal (mm) | Mean sum of erythema (mm) | Range of sum of erythema (mm)
11 | 14.272 | 9-20 | 60.727 | 41.92

b. Patients tested only by the intradermal method:

Intradermal tests (using 0.05mL) on 11 puncture positive patients BAU/mL to elicit 50mm sum of dia. of erythema reaction

# Persons | Mean | Range
11 | 0.019 | 0.8-0.0032

INDICATIONS AND USAGE

Standardized Cat Hair is intended for use in the diagnosis and therapy of cat allergy patients as established by allergy history and skin test reactivity.

CONTRAINDICATIONS

Standardized Cat Hair extract should not be used if the patient has asthma, cardiovascular disease, emphysema, diabetes, bleeding diathesis or pregnancy, unless a specific diagnosis of Type 1 allergy to cat is made based on skin testing and the benefits of treatment outweigh the risks of an adverse reaction during testing or treatment. Cat extract is not indicated for use in patients who are not clinically allergic to cat or who are not skin reactive to cat allergenic extract. Limitations on treatment should be considered when treating young, or geriatric patients or patients suffering from auto-immune disorders or severe and unstable allergic disorders.

WARNINGS

Standardized Cat Hair extract is NOT interchangeable with standardized cat pelt extracts or standardized cat extracts labeled in AU/mL or non-standardized cat extracts.

Concentrated extracts must be diluted with sterile diluent prior to first use on a patient for treatment or intradermal testing.

DO NOT INJECT INTRAVENOUSLY This product should not be injected intravenously. Deep subcutaneous routes have proven to be safe. All concentrates of allergenic extracts have the ability to cause serious local and systemic reactions including death in sensitive patients.(10) Sensitive patients may experience severe anaphylactic reactions resulting in respiratory obstruction, shock, coma and/or death.

An allergenic extract should be temporarily withheld from patients or the dose of the extract adjusted downward if any of the following conditions exist: (1) Severe symptoms of rhinitis and/or asthma (2) Infections or flu accompanied by fever (3) Exposure to excessive amounts of clinically relevant allergen prior to a scheduled injection.

PRECAUTIONS

General Information:

Epinephrine 1:1000 should be available as well as personnel trained in administering emergency treatment. Allergenic extracts are not intended for intravenous injection. For safe and effective use of allergenic extracts, sterile solutions, vials, syringes, etc. should be used and aseptic precautions observed in making dilutions and administering the allergenic extract injection. A sterile tuberculin syringe graduated in 0.1 mL units to measure each dose for the prescribed dilution should be used.

To reduce the risk of an occurrence of adverse reactions, begin with a careful personal and family history plus a physical exam. Confirm your findings with scratch or intradermal skin testing. Patients should be observed for 30 minutes after any test.

Information for Patients: All concentrates of allergenic extracts have the ability to cause serious local and systemic reactions including death in sensitive patients. To minimize this potential hazard, the relative sensitivity of the patient must be assessed from the allergic history and from clinical observations. In certain individuals, life-threatening reactions may occur. Patients should be informed of this risk prior to skin testing and immunotherapy. Patients should be instructed to recognize adverse reaction symptoms that may occur and to report all adverse reactions to a physician. Patients should be told to wait in the office after injections for at least 30 minutes.

Drug Interactions: Antihistamines and Hydroxyzine can significantly inhibit the immediate skin test reactions as they tend to neutralize or antagonize the action of histamine.(11) This effect has been primarily documented when testing was performed within 1 to 2 hours after drug ingestion. Although partial inhibition of the skin test reaction had been observed for longer periods, it was minor. Epinephrine injection inhibits the immediate skin test reactions for several hours. Patients on delayed absorption antihistamine tablets should be free of such medication for 48 hours before testing. Patients using Astemizole (Hismanal) may experience prolonged suppression and should be free from such medication for up to 6 to 8 weeks prior to testing. Refer to package insert from long acting antihistamine manufacturer for more information.

Extreme caution should be taken when using allergenic extracts on patients who are taking beta-blockers. Patients receiving beta-blockers may not be responsive to epinephrine or inhaled bronchodialators.

Carcinogenesis, mutagenesis, impairment of fertility:

Long term studies in animals have not been conducted with allergenic extracts, including standardized Cat Hair extracts, to determine their potential carcinogenicity, mutagenicity or impairment of fertility.

Pregnancy: Category C: Animal reproduction studies have not been conducted with standardized Cat Hair extract. It is not known whether this extract can cause fetal harm when administered to pregnant women or can effect reproduction capacity. Standardized Cat Hair extract should be used for pregnant women only if clearly needed.

Nursing Mothers: It is not known whether this drug appears in human milk. Because many drugs are detectable in human milk, caution should be exercised when Allergenic Extract, Standardized Cat Hair, is administered to a nursing woman. There are no current studies on extract components in human milk, or their effect on the nursing infant.

Pediatric Use: Allergenic extracts have been used in children over two years of age. It is recommended that children be treated only when indicated. (7)

ADVERSE REACTIONS

Adverse systemic reactions usually occur within minutes and consist primarily of allergic symptoms such as: generalized skin erythema, urticaria, pruritus, angioedema, rhinitis, induced asthma, itching of nose or throat, wheezing, laryngeal edema, dyspnea, coughing, marked perspiration and hypotension. Less commonly, nausea, emesis, abdominal cramps, diarrhea and uterine contractions may occur. Severe reactions may cause anaphylaxis or shock and loss of consciousness. Fatalities have occurred rarely.(12) To some extent, the reaction rate is related to the type and dose of administered extract and to the degree of sensitivity of the patient.

The treatment of systemic allergic reactions is dependent upon the symptom complex. Antihistamines may offer relief of recurrent urticaria, associated skin reactions and gastrointestinal symptoms. Corticosteroids may provide benefit if symptoms are prolonged or recurrent. (See Overdosage)

Local reactions consisting of erythema, itching, swelling tenderness and sometimes pain may occur at the injection site. These reactions may appear within a few minutes to hours and persist for several days. Local cold applications and oral antihistamines may be effective treatment for local reactions. For marked and prolonged local reactions steroids may be helpful.

Serious adverse reactions should be reported to Nelco Laboratories immediately and a report can be filed to MedWatch, The FDA Medical Product Problem Reporting Program, at 5600 Fishers Lane, Rockville, MD 20852-9787, call 1-800-FDA-1088.

OVERDOSAGE

Overdosage can cause both local and systemic reactions. An overdose may be prevented by careful observation and questioning of the patient about the previous injection. If systemic or anaphylactic reaction does occur, apply a tourniquet above the site of injection and inject intramuscularly or subcutaneously 0.3 to 0.5mL of 1:1000 epinephrine hydrochloride into the opposite arm. The dose may be repeated in 5-10 minutes if necessary. Loosen the tourniquet at least every 10 minutes. The epinephrine hydrochloride 1:1000 dose for infants to 2 years is 0.05 to 0.1 mL; for children 2 to 6 years it is 0.15mL; for children 6-12 years it is 0.2mL.

Patients unresponsive to epinephrine may be treated with theophylline. Studies on asthmatic subjects reveal that plasma concentrations of Theophylline of 5 to 20 µg/mL are associated with therapeutic effects. Toxicity is particularly apparent at concentrations greater than 20 µg/mL. A loading dose of Aminophylline of 5.8 mg/kg intravenously followed by 0.9 mg/kg per hour results in plasma concentrations of approximately 10 µg/mL (for patients not previously receiving theophylline). (Mitenko and Ogilive 1773; Nicholoson and Chick 1973)

Maintenance of a patient airway is critical if upper or lower airway obstruction is present. Other beta-adrenergic drugs such as Isoproterenol, Isoetharine, or Albuterol may be used by inhalation. The usual dose to relieve broncho-constriction in asthma is 0.5 mL of the 0.5% solution for Isoproterenol HCl. The Albuterol inhaler delivers approximately 90 mcg of Albuterol from the mouthpiece. The usual dosage for adults and children would be two inhalations repeated every 4-6 hours. Isoetharine supplied in the Bronkometer unit delivers approximately 340 mcg Isoetharine. The average dose is one to two inhalations. Persistent wheezing may necessitate intravenous aminophylline treatment. For profound shock and hypotension, intravenous fluids, vasopressors and oxygen may also be needed. Respiratory obstruction not responding to parenteral or inhaled bronchodilators may require Theophylline, oxygen, intubation and the use of life support systems.

DOSAGE AND ADMINISTRATION

It is imperative that the physician determine the initial dose of the product by skin testing. Patients being switched from extracts not labeled in Bioequivalency Allergy Units should be started as if they were coming under treatment for the first time. Patients being switched from one lot of Standardized Cat Hair to another lot of Standardized Cat Hair (from the same or different manufacturers) should have the initial dose from the new lot reduced by 75%. Patients being switched from a Standardized Cat Pelt extract to a Standardized Cat Hair extract (both labeled in BAU/mL) should be skin tested with both extracts to determine the relative potency of the extracts and the dosage adjusted accordingly.

Recommended usual dosage and range: (Scratch or Prick Testing)

The general method of making a scratch test is to first scarify the skin and then apply a drop of extract to the scratch. Make scarifications at least 2.5 cm apart. Hold the scarifier between thumb and index finger, press the sharp edge of the instrument against the skin and twirl instrument rapidly. The scratch should disrupt the outer layers of epidermis but should not produce immediate oozing of blood. One drop (0.05 mL) of extract is rubbed or applied into each scratch. Always apply a control scratch with each test set. Sterile Diluting fluid (for a negative control) is used in exactly the same way as an active test extract. Histamine may be used as a positive control. Scratch or prick test sites should be examined at 15 and 30 minutes. To prevent excessive absorption, wipe off antigens producing large reactions as soon as the wheal appears. Record the size of the reaction.

Recommended usual dosage and range: (Intradermal Testing)

Patients with a negative scratch or prick-puncture test:

Patients who do not react to a valid scratch or prick- puncture test should be tested intradermally with a 0.05 mL of a 50 BAU/mL extract solution. If this test is negative, a second intradermal test may be performed using a 100 BAU/mL extract dilution. The negative puncture control must be diluted appropriately for intradermal use. .

To prepare a 50 BAU/mL dilution from 10,000 BAU/mL vial:

Take 5.0 mL of the 10,000 BAU/mL + 5.0 mL of diluent =Vial A @5,000 BAU/mL.

Take 1.0 of vial A + 9.0 mL diluent = vial B @500 BAU/mL.

Take 1.0 of vial B + 9.0 mL diluent = vial C @50 BAU/mL.

Patients being suspected of being highly allergic should be tested with 0.05 mL of a 0.1 BAU/mL dilution. A negative test should be followed by repeat tests using progressively stronger concentrations until the maximal recommended strength of 100 BAU/mL is reached. The negative puncture test control must be diluted appropriately for intradermal use. To prepare this dilution follow the tenfold dilution series chart for therapeutic allergens.

Allergic response is based on measurement of wheal and erythema with respect to positive and negative control skin tests. Skin tests are graded in terms of the wheal and erythema response noted at 10 to 20 minutes. Wheal and erythema size may be recorded by actual measurement or the extent of both responses.

Recommended dosage and range: (Therapeutic) Dosage of allergenic extracts is a highly individualized matter and varies according to the degree of sensitivity of the patient, and the clinical response and tolerance to the extract administered during the injection regimen. The dosage of allergenic extract does not vary significantly with the respiratory allergic disease under treatment.

In patients who appear to be highly sensitive by history and skin test, the initial dose of the extract should be 0.05mL of 0.01 to 0.1 BAU/mL. Patients with lesser sensitivity may be started using 1.0 BAU/mL. The amount of allergenic extract is increased at each injection by not more than 50%-100% of the previous amount, and the next increment is governed by the response to the last injection.

Any evidence of systemic reaction is an indication for a significant reduction (at least 50%) in the subsequent dose. Any evidence of a local or generalized reaction requires a reduction in dosage. After therapeutic injections patients should always be observed for at least 30 minutes. If adverse reactions appear, the next therapeutic injection of extract should be reduced to the dose which does not elicit a reaction and subsequent doses increased more slowly. The upper limits of dosage have not been established. Doses larger than 0.2 mL of 10,000 BAU/mL may be painful due to glycerin content. (9)

Preparation Instructions To prepare a dilution for intradermal and therapeutic use, one starts with 10,000 BAU/mL stock concentrate and makes a 1:10 dilution by adding 1.0 mL of the concentrate to 9.0 mL of sterile diluent. Subsequent dilutions are made in similar manner.

TEN-FOLD DILUTION SERIES
Dilution | Extract | Diluent mL | BAU/mL
0 | Concentrate | 0 | 10,000
1 | 1mL concentrate | 9 | 1,000
2 | 1mL dilution #1 | 9 | 100
3 | 1mL dilution #2 | 9 | 10
4 | 1mL dilution #3 | 9 | 1
5 | 1mL dilution #4 | 9 | 0.1
6 | 1mL dilution #5 | 9 | 0.01

Intervals between doses: The optimal interval between doses of allergenic extract has not been definitely established. However, as it is customary practiced, injections are given once or twice per week until the maintenance dose of extract is reached. At this time, the injection interval may be increased to 2 weeks, then 3 weeks and finally to 4 weeks. If the patient does not return for 6-8 weeks after the last injection, the dose should be reduced to 25% of the last dose. If longer than 8 weeks, a dose reduction of 1,2, or 3 dilution's may be made depending on a consideration of the components and the patient's sensitivity. The dosage and the interval between injections may need to be modified according to the clinical response of the patient. When switching patients to a fresh extract the initial dose should be reduced 3/4 so that 25% of previous dose is administered.

Duration of treatment: The usual duration of treatment has not been established. A period of two or three years of injection therapy constitutes an average minimum course of treatment.

Parenteral drug products should be inspected visually for particulate matter and discoloration prior to administration, whenever solution and container permit.

HOW SUPPLIED

Diagnostic Allergens:

Scratch or Prick test:

10,000 BAU/mL in 50% glycerin (v/v) in 5mL dropper vials.

Intradermal test:

100 BAU/mL in 5mL or 10mL sterile multiple dose vials.

Concentrate of Extract for Therapeutic Use Allergens:

10,000 BAU/mL or special dilution according to prescription, are contained in 5mL, 10mL, 50mL multiple dose vials.

Dilutions of concentrate of allergenic extracts can be made with either buffered diluent containing 0.4% phenol or with diluent containing 50% glycerin (v/v) with salts.

STORAGE

The expiration date of Standardized Cat Hair extract containing 10,000 BAU/mL in 50% glycerin (v/v) is listed on the container label. Store extracts at 2° to 8° C and keep them in this range during office use.

WARRANTY: We warrant that this product was prepared and tested according to the standards of the FDA and is true to label. Because of biological differences in individuals and because allergenic extracts are manufactured to be potent and because we have no control over the conditions of use, we cannot and do not warrant either a good effect or against an ill effect following use.

REFERENCES

1. Ohman, J.L., Studies on the origin and environmental occurrence of Cat allergen, J. Allergy Clin.Immunol., 69:127, 1982.

2. Ohman,J.L., Baer, H., Anderson, M.C., Leiterman,K., Brown, P. Surface washes of living cats:An improved method of obtaining clinically relevant allergen. J.Allergy Clin.Immunol. 2:3, 288-293, 1983.

3. Anderson, M.C., Baer,H., Allergenically active components of cat allergen extracts. Journal of Immunol: 127, 3, 972-975, 1981.

4. Dabrowski,A.J., VanDerBrempt,X., Soler,M., Seguret,N., Lucciani,P., Charpin,D., Vervloet,D., Cat skin as an important source of Fel d 1 allergen. J. Allergy Clin.Immunol: 86,4, 462-465, 1990.

5. In vitro Test Methods, Radial Immunodiffusion (RID) Fel d 1 Cat Allergen Methods & Procedures Manual, CBER, 1993.

6. Quantitative Intradermal Procedure for Evaluation of Subject Sensitivity to Standardized Allergenic Extracts and for Assignment of Bioequivalent Allergy Units to Reference Preparations using the ID50EAL method. Methods & Procedures Manual, CBER, 1993.

7. Murray,A.B., Ferguson,A.C., Morrison,B.J., The frequency and severity of cat allergy vs dog allergy in atopic children. J.Allergy Clin. Immunol:72, 145-9, 1983.

8. Taylor, W.W., Ohman, J.L., Lowell,F.C., Immunotherapy in cat induced asthma: Double blind trial with evaluation of bronchial responses to cat allergen and histamine. J.Allergy Clin. Immunol., 61:283-87, 1978.

9. Ohman,J.C., Findlay, S.R., Leiterman,K., Immunotherapy in cat induced asthma: Double blind trial with evaluations of in vivo and in vitro responses. J.Allergy Clin.Immunol., 74:230, 1984.

10. Middleton, Reed & Ellis, Allergy Principles and Practice. p.222, Mosby, St.Louis,1978.

11. Lockey,R.F, Bukantz SC, et al. Allergen Immunotherapy. New York, NY : Marcel Dekker Inc. 1991.

12. Reid,M.J., Lockey,R.F., Turkeltaub,P.C., Platts-Mills,T.A.E., Survey of fatalities from skin testing and immunotherapy 1985-1989. Journal of Allergy Clin. Immunol. 92 (1): 6-15, July 1993.